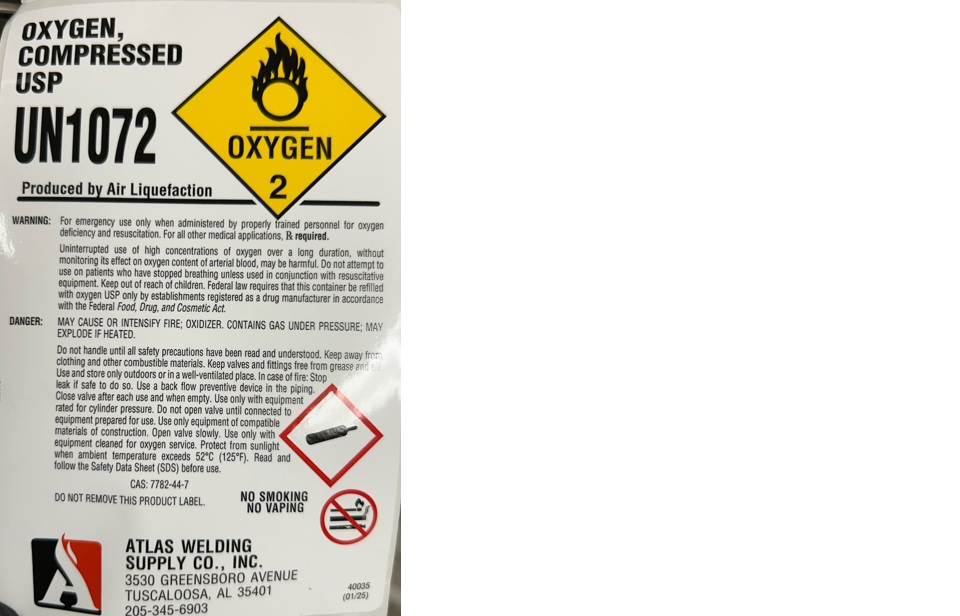 DRUG LABEL: Oxygen
NDC: 51051-003 | Form: GAS
Manufacturer: Atlas Welding Supply Company, Inc.
Category: prescription | Type: HUMAN PRESCRIPTION DRUG LABEL
Date: 20251223

ACTIVE INGREDIENTS: OXYGEN 990 mL/1 L

Oxygen

PACKAGE LABEL

OXYGEN, COMPRESSED USP

UN1072

Produced by Air Liquefaction

WARNING: For emergency use only when administered by properly trained personnel for oxygen deficiency and resuscitation. For all other medical applications, Rx required

Uninterrupted use of high concentrations of oxygen over a long duration, without monitoring its effect on oxygen content of arterial blood, may be harmful. Do not attempt to use on patients who have stopped breathing unless used in conjunction with resuscitative equipment. Keep out of reach of children. Federal law requires that this container be refilled with oxygen USP only by establishments registered as a drug manufacturer in accordance with the Federal Food, Drug, and Cosmetic Act.

DANGER: MAY CAUSE OR INTENSIFY FIRE; OXIDIZER. CONTAINS GAS UNDER PRESSURE; MAY EXPLODE IF HEATED.

Do not handle until all safety precautions have been read and understood. Keep away from clothing and other combustible materials. Keep valves and fittings free from grease and oil. Use and store only outdoors or in a well-ventilated place. In case of fire: Stop leak if safe to do so. Use a back flow preventive device in the piping. Close valve after each use and when empty. Use only with equipment rated for cylinder pressure. Do not open valve until connected to equipment prepared for use. Use only equipment of compatible materials of construction. Open valve slowly. Use only with equipment cleaned for oxygen service. Protect from sunlight when ambient temperature exceeds 52 C (125 F). Read and follow the Safety Data Sheet (SDS) before use.

CAS: 7782-44-7

DO NOT REMOVE THIS PRODUCT LABEL.

NO SMOKING

NO VAPING

ATLAS WELDING SUPPLY CO., INC.

3530 GREENSBORO AVENUE

TUSCALOOSA, AL 35401

205-345-6903